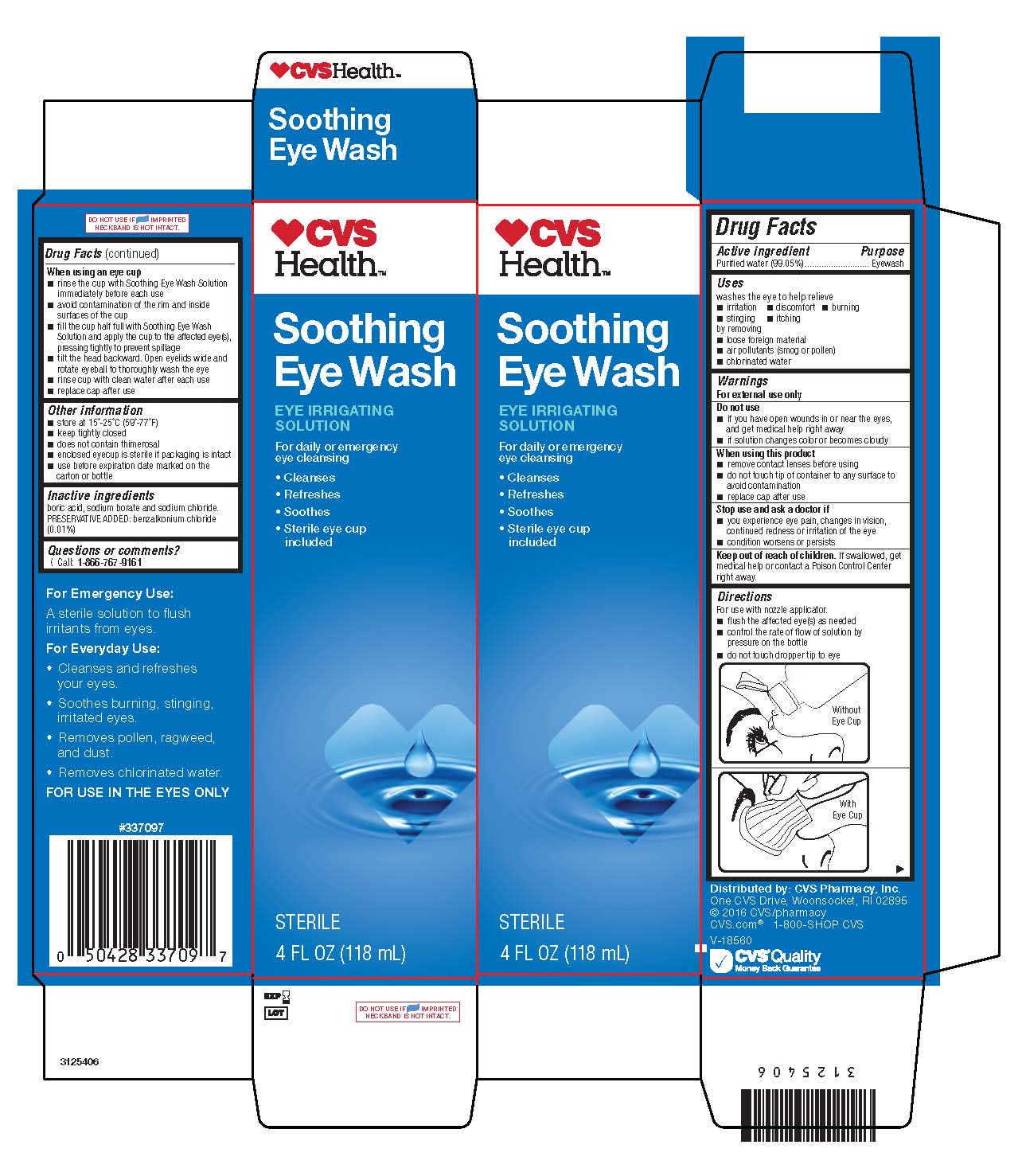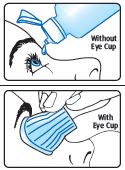 DRUG LABEL: Eye Wash
NDC: 59779-337 | Form: SOLUTION
Manufacturer: CVS Pharmacy
Category: otc | Type: HUMAN OTC DRUG LABEL
Date: 20170329

ACTIVE INGREDIENTS: WATER 99.05 mL/100 mL
INACTIVE INGREDIENTS: BORIC ACID; SODIUM BORATE; SODIUM CHLORIDE; BENZALKONIUM CHLORIDE

Drug Facts

Active ingredient

Purified water (99.05%)

Purpose

Eyewash

Uses

washes the eye to help relieve

- irritation
- stinging
- discomfort
- itching
- burning

by removing

- loose foreign material
- air pollutants (smog or pollen)
- chlorinated water

Warnings

For external use only

Do not use

- if you have open wounds in or near the eyes, and get medical help right away
- if solution changes color or becomes cloudy

When using this product

- remove contact lenses before using
- do not touch tip of container to any surface to avoid contamination
- replace cap after use

Stop use and ask a doctor if

- you experience eye pain, changes in vision, continued redness or irritation of the eye
- condition worsens or persists

Keep out of reach of children.

If swallowed, get medical help or contact a Poison Control Center right away.

Directions

For use with a nozzle applicator.

- flush the affected eye(s) as needed
- control the rate of flow of solution by pressure on the bottle
- do not touch dropper tip to eye

When using an eye cup

- rinse the cup with Soothing Eye Wash Solution
  immediately before each use
- avoid contamination of the rim and inside
  surfaces of the cup
- fill the cup half full with Soothing Eye Wash
  Solution and apply the cup to the affected eye(s),
  pressing tightly to prevent spillage

Other information

- store at 15°-25°C (59°-77°F)
- keep tightly closed
- does not contain thimerosal
- enclosed eyecup is sterile if packaging is intact
- use before expiration date marked on the
  carton or bottle

Inactive ingredients

boric acid, sodium borate and sodium chloride. PRESERVATIVE ADDED: benzalkonium chloride

(0.01%)

Questions or comments?

Call: 1-866-767-9161

Package/Label Principal Display Panel

CVS
Health™

Soothing

Eye Wash

EYE IRRIGATING

SOLUTION

For daily or emergency

eye cleansing

• Cleanses

• Refreshes

• Soothes

• Sterile eye cup

included

[icon] blue heart with drop inside

STERILE

4 FL OZ (118 mL)